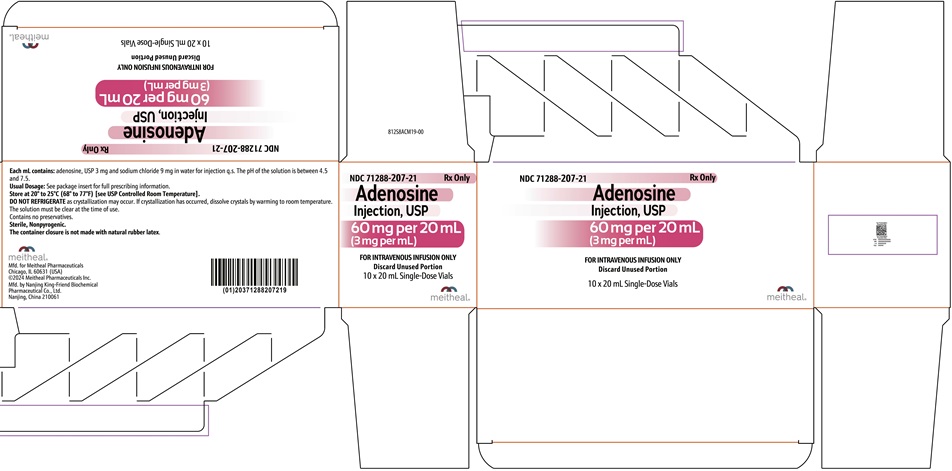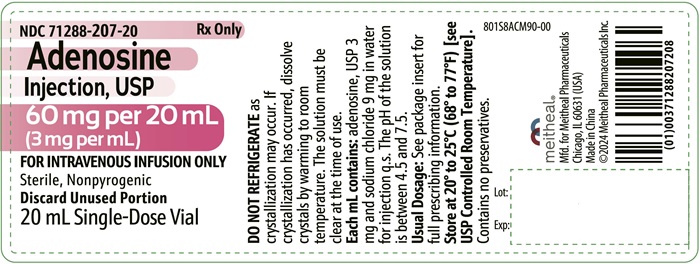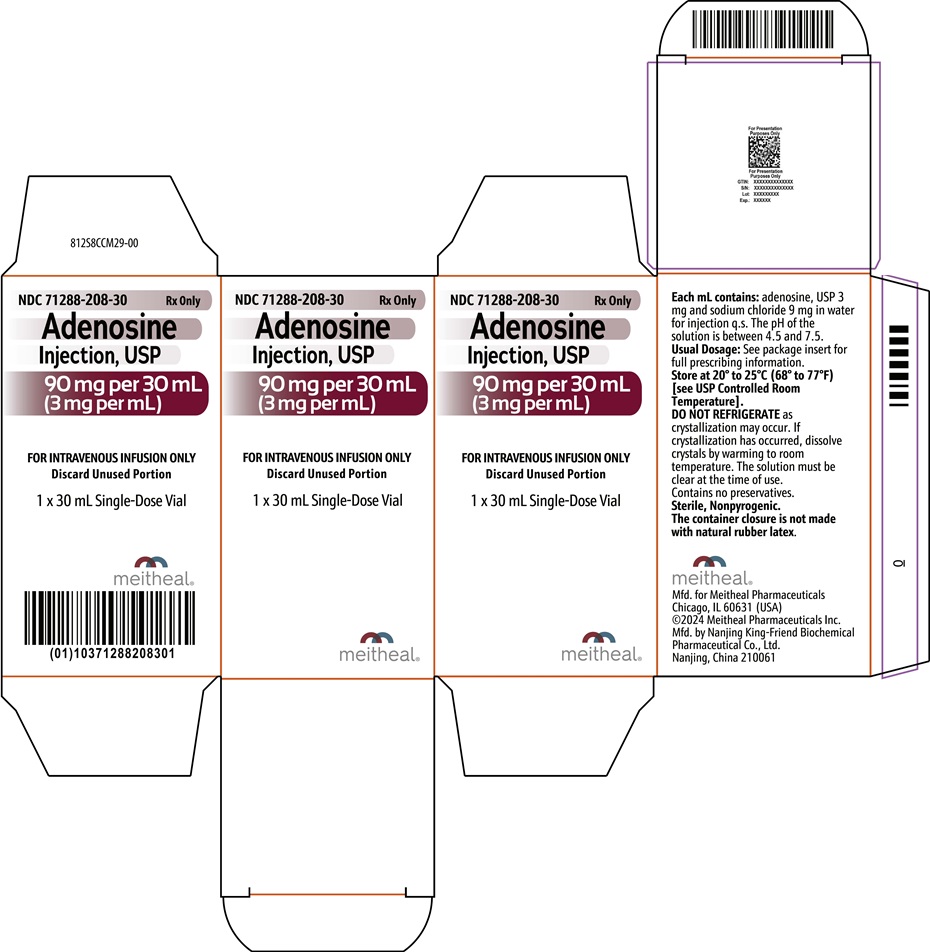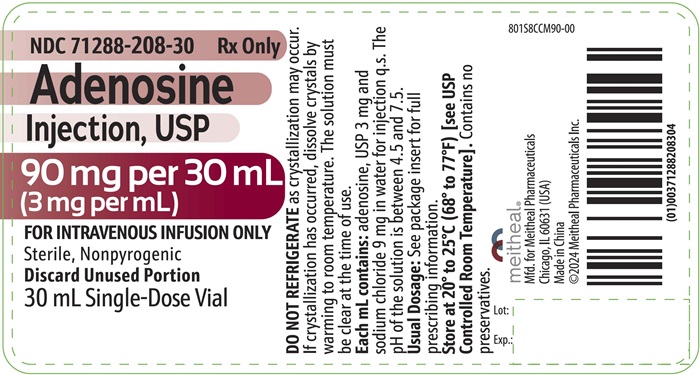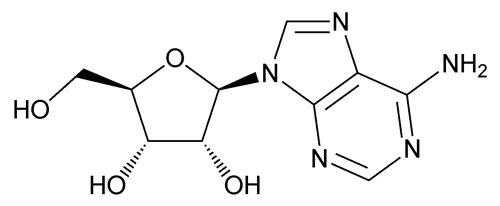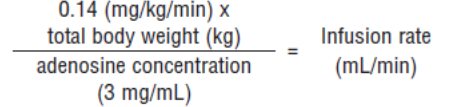 DRUG LABEL: Adenosine
NDC: 71288-207 | Form: INJECTION, SOLUTION
Manufacturer: Meitheal Pharmaceuticals Inc.
Category: prescription | Type: HUMAN PRESCRIPTION DRUG LABEL
Date: 20250414

ACTIVE INGREDIENTS: ADENOSINE 3 mg/1 mL
INACTIVE INGREDIENTS: SODIUM CHLORIDE; WATER

HIGHLIGHTS OF PRESCRIBING INFORMATION

These highlights do not include all the information needed to use ADENOSINE INJECTION safely and effectively. See full prescribing information for ADENOSINE INJECTION.
ADENOSINE injection, for intravenous use
Initial U.S. Approval: 1995

1 INDICATIONS AND USAGE

Adenosine injection, a pharmacologic stress agent, is indicated as an adjunct to thallium-201 myocardial perfusion scintigraphy in patients unable to exercise adequately (1)

2 DOSAGE AND ADMINISTRATION

Recommended dose is 0.14 mg/kg/min infused over six minutes as a continuous peripheral intravenous infusion (total dose of 0.84 mg/kg) (2)

3 DOSAGE FORMS AND STRENGTHS

Injection: 60 mg per 20 mL (3 mg per mL) and 90 mg per 30 mL (3 mg per mL) in single-dose vials (3)

4 CONTRAINDICATIONS

- Second- or third-degree AV block (except in patients with a functioning artificial pacemaker) (4)
- Sinus node disease, such as sick sinus syndrome or symptomatic bradycardia (except in patients with a functioning artificial pacemaker) (4)
- Known or suspected bronchoconstrictive or bronchospastic lung disease (e.g., asthma) (4)
- Known hypersensitivity to adenosine (4)

5 WARNINGS AND PRECAUTIONS

- Cardiac Arrest, Ventricular Arrhythmias, and Myocardial Infarction. Fatal cardiac events have occurred. Avoid use in patients with symptoms or signs of acute myocardial ischemia. Appropriate resuscitative measures should be available (5.1)
- Sinoatrial (SA) and Atrioventricular (AV) Nodal Block. First-, second- or third-degree AV block, or sinus bradycardia can occur. Discontinue adenosine if patient develops persistent or symptomatic high-grade AV block (5.2)
- Bronchoconstriction. Can induce dyspnea, bronchoconstriction, and respiratory compromise, especially in patients with obstructive pulmonary disease. Discontinue adenosine if patient develops severe respiratory difficulties (5.3)
- Hypotension. Significant hypotension can occur. Discontinue adenosine if patient develops persistent or symptomatic hypotension (5.4)
- Cerebrovascular Accidents. Hemorrhagic and ischemic cerebrovascular accidents have occurred (5.5)
- Seizures. New onset or recurrence of convulsive seizures have occurred. Use of methylxanthines (e.g., caffeine, aminophylline and theophylline) is not recommended in patients who experience a seizure in association with adenosine (5.6)
- Hypersensitivity. Dyspnea, throat tightness, flushing, erythema, rash, and chest discomfort have occurred. Have personnel and resuscitative equipment immediately available (5.7)
- Atrial Fibrillation. Reported in patients with or without a history of atrial fibrillation (5.8)
- Hypertension. Clinically significant increases in systolic and diastolic pressure have been observed (5.9)

6 ADVERSE REACTIONS

Most common adverse reactions (incidence ≥ 10%) are: flushing; chest discomfort; shortness of breath; headache; throat, neck or jaw discomfort; gastrointestinal discomfort; and dizziness (6.1)

To report SUSPECTED ADVERSE REACTIONS, contact Meitheal Pharmaceuticals, Inc. at 1-844-824-8426 or FDA at 1-800-FDA-1088 or www.fda.gov/medwatch.

7 DRUG INTERACTIONS

- Methylxanthines interfere with the activity of adenosine (7.1, 10)
- Nucleoside transport inhibitors such as dipyridamole can increase the activity of adenosine (7.1)

FULL PRESCRIBING INFORMATION

1 INDICATIONS AND USAGE

Adenosine injection is indicated as an adjunct to thallium-201 myocardial perfusion scintigraphy in patients unable to exercise adequately.

2 DOSAGE AND ADMINISTRATION

The recommended adenosine injection dose is 0.14 mg/kg/min infused over six minutes (total dose of 0.84 mg/kg) (Table 1).

- Administer adenosine injection only as a continuous peripheral intravenous infusion
- Inject Thallium-201 at the midpoint of the adenosine injection infusion (i.e., after the first three minutes of adenosine injection)
- Thallium-201 is physically compatible with adenosine injection and may be injected directly into the adenosine injection infusion set
- Inject Thallium-201 as close to the venous access as possible to prevent an inadvertent increase in the dose of adenosine injection (the contents of the intravenous tubing) being administered

Visually inspect adenosine injection for particulate matter and discoloration prior to administration. Do not administer adenosine injection if it contains particulate matter or is discolored.

There are no data on the safety or efficacy of alternative adenosine injection infusion protocols. The safety and efficacy of adenosine injection administered by the intracoronary route have not been established.

Table 1 Dosage Chart for Adenosine Injection

Patient Weight (kilograms) | Infusion Rate (mL per minute over 6 minutes for total dose of; 0.84 mg/kg)
45 | 2.1
50 | 2.3
55 | 2.6
60 | 2.8
65 | 3
70 | 3.3
75 | 3.5
80 | 3.8
85 | 4
90 | 4.2

The nomogram displayed in Table 1 was derived from the following general formula:

3 DOSAGE FORMS AND STRENGTHS

Injection: 60 mg per 20 mL (3 mg per mL) and 90 mg per 30 mL (3 mg per mL) in single-dose vials containing a sterile, nonpyrogenic, clear, colorless solution of adenosine, USP.

4 CONTRAINDICATIONS

Adenosine is contraindicated in patients with:

- Second- or third-degree AV block (except in patients with a functioning artificial pacemaker) [see Warnings and Precautions (5.2)]
- Sinus node disease, such as sick sinus syndrome or symptomatic bradycardia (except in patients with a functioning artificial pacemaker) [see Warnings and Precautions (5.2)]
- Known or suspected bronchoconstrictive or bronchospastic lung disease (e.g., asthma) [see Warnings and Precautions (5.3)]
- Known hypersensitivity to adenosine [see Warnings and Precautions (5.7)]

5 WARNINGS AND PRECAUTIONS

5.1 Cardiac Arrest, Ventricular Arrhythmias, and Myocardial Infarction

Fatal and nonfatal cardiac arrest, sustained ventricular tachycardia (requiring resuscitation), and myocardial infarction have occurred following adenosine infusion. Avoid use in patients with symptoms or signs of acute myocardial ischemia, for example, unstable angina or cardiovascular instability; these patients may be at greater risk of serious cardiovascular reactions to adenosine. Appropriate resuscitative measures should be available [see Overdosage (10)].

5.2 Sinoatrial and Atrioventricular Nodal Block

Adenosine exerts a direct depressant effect on the SA and AV nodes and may cause first-, second- or third-degree AV block, or sinus bradycardia. In clinical trials, approximately 6% of patients developed AV block following adenosine administration (first-degree heart block developed in 3%, second-degree in 3%, and third-degree in 0.8% of patients) [see Clinical Trials Experience (6.1)].
Use adenosine with caution in patients with pre-existing first-degree AV block or bundle branch block. Do not use in patients with high-grade AV block or sinus node dysfunction (except in patients with a functioning artificial pacemaker). Discontinue adenosine in any patient who develops persistent or symptomatic high-grade AV block.

5.3 Bronchoconstriction

Adenosine administration can cause dyspnea, bronchoconstriction, and respiratory compromise. Adenosine should be used with caution in patients with obstructive lung disease not associated with bronchoconstriction (e.g., emphysema, bronchitis). Do not use in patients with bronchoconstriction or bronchospasm (e.g., asthma). Discontinue adenosine in any patient who develops severe respiratory difficulties. Resuscitative measures should be available prior to adenosine administration [see Clinical Trials Experience (6.1), Overdosage (10), and Clinical Pharmacology (12.2)].

5.4 Hypotension

Adenosine is a potent peripheral vasodilator and can induce significant hypotension. The risk of serious hypotension may be higher in patients with autonomic dysfunction, hypovolemia, stenotic valvular heart disease, pericarditis or pericardial effusions, or stenotic carotid artery disease with cerebrovascular insufficiency. Discontinue adenosine in any patient who develops persistent or symptomatic hypotension.

5.5 Cerebrovascular Accident

Hemorrhagic and ischemic cerebrovascular accidents have occurred. Hemodynamic effects of adenosine including hypotension or hypertension can be associated with these adverse reactions [see Warnings and Precautions (5.4) and (5.9)].

5.6 Seizures

New-onset or recurrence of convulsive seizures has occurred following adenosine. Some seizures are prolonged and require emergent anticonvulsive management. Aminophylline may increase the risk of seizures associated with adenosine. Methylxanthine use is not recommended in patients who experience seizures in association with adenosine administration [see Overdosage (10)].

5.7 Hypersensitivity

Dyspnea, throat tightness, flushing, erythema, rash, and chest discomfort have occurred. Symptomatic treatment may be required. Have personnel and appropriate treatment available. Resuscitative measures may be necessary if symptoms progress [see Post-Marketing Experience (6.2)].

5.8 Atrial Fibrillation

Adenosine can cause atrial fibrillation in patients with or without a history of atrial fibrillation. Atrial fibrillation typically began 1.5 to 3 minutes after initiation of adenosine, lasted for 15 seconds to 6 hours, and spontaneously converted to normal sinus rhythm [see Post-Marketing Experience (6.2)].

5.9 Hypertension

Adenosine can induce clinically significant increases in systolic and diastolic blood pressure. Most increases resolved spontaneously within several minutes, but in some cases, hypertension lasted for several hours [see Clinical Trials Experience (6.1)].

6 ADVERSE REACTIONS

The following adverse reactions are discussed in more detail in other sections of the prescribing information:

- Fatal Cardiac Arrest, Ventricular Arrhythmias, and Myocardial Infarction [see Warnings and Precautions (5.1)]
- Sinoatrial and Atrioventricular Nodal Block [see Warnings and Precautions (5.2)]
- Bronchoconstriction [see Warnings and Precautions (5.3)]
- Hypotension [see Warnings and Precautions (5.4)]
- Cerebrovascular Accident [see Warnings and Precautions (5.5)]
- Seizures [see Warnings and Precautions (5.6)]
- Hypersensitivity [see Warnings and Precautions (5.7)]
- Atrial fibrillation [see Warnings and Precautions (5.8)]
- Hypertension [see Warnings and Precautions (5.9)]

6.1 Clinical Trials Experience

Because clinical trials are conducted under widely varying conditions, adverse reaction rates observed in the clinical trials of a drug cannot be directly compared to rates in the clinical trials of another drug and may not reflect the rates observed in practice.
The following adverse reactions, with an incidence of at least 1%, were reported with adenosine among 1,421 patients in clinical trials. 11% of the adverse reactions occurred several hours after adenosine administration. 8% of the adverse reactions began with adenosine infusion and persisted for up to 24 hours.

The most common (incidence ≥ 10%) adverse reactions to adenosine are flushing, chest discomfort, shortness of breath, headache, throat, neck or jaw discomfort, gastrointestinal discomfort, and dizziness (Table 2).

Table 2 Adverse Reactions in Clinical Trials (Frequency ≥ 1%)

Adverse Reactions | Adenosine; N=1,421
Flushing | 44%
Chest discomfort | 40%
Dyspnea | 28%
Headache | 18%
Throat, neck or jaw discomfort | 15%
Gastrointestinal discomfort | 13%
Lightheadedness/dizziness | 12%
Upper extremity discomfort | 4%
ST segment depression | 3%
First-degree AV block | 3%
Second-degree AV block | 3%
Paresthesia | 2%
Hypotension | 2%
Nervousness | 2%
Arrhythmias | 1%

Adverse reactions to adenosine of any severity reported in less than 1% of patients include:

Body as a Whole: | back discomfort, lower extremity discomfort, weakness
Cardiovascular System: | myocardial infarction, ventricular arrhythmia, third-degree AV block, bradycardia, palpitation, sinus exit block, sinus pause, T-wave changes, hypertension (systolic blood pressure > 200 mm Hg)
Respiratory System: | cough
Central Nervous System: | drowsiness, emotional instability, tremors
Genital/Urinary System: | vaginal pressure, urgency
Special Senses: | blurred vision, dry mouth, ear discomfort, metallic taste, nasal congestion, scotomas, tongue discomfort

6.2 Post-Marketing Experience

The following adverse reactions have been reported from marketing experience with adenosine. Because these reactions are reported voluntarily from a population of uncertain size, are associated with concomitant diseases and multiple drug therapies and surgical procedures, it is not always possible to reliably estimate their frequency or establish a causal relationship to drug exposure.

Cardiac Disorders: | cardiac arrest, atrial fibrillation, cardiac failure, myocardial infarction, tachycardia, ventricular arrhythmia
Gastrointestinal Disorders: | nausea and vomiting
General Disorders and Administration Site Conditions: | chest pain, injection site reaction, infusion site pain
Immune System Disorders: | hypersensitivity
Nervous System Disorders: | cerebrovascular accident including intracranial hemorrhage, seizure activity including tonic-clonic (grand mal) seizures, loss of consciousness
Respiratory, Thoracic and Mediastinal Disorders: | bronchospasm, respiratory arrest, throat tightness

7 DRUG INTERACTIONS

7.1 Effects of Other Drugs on Adenosine

- The vasoactive effects of adenosine are inhibited by adenosine receptor antagonists, (such as methylxanthines (e.g., caffeine, aminophylline, and theophylline). The safety and efficacy of adenosine in the presence of these agents has not been systematically evaluated [see Overdosage (10)].
- The vasoactive effects of adenosine are potentiated by nucleoside transport inhibitors such as dipyridamole. The safety and efficacy of adenosine in the presence of dipyridamole has not been systematically evaluated.
- Whenever possible, drugs that might inhibit or augment the effects of adenosine should be withheld for at least five half-lives prior to the use of adenosine.

7.2 Effects of Adenosine on Other Drugs

Adenosine injection has been given with other cardioactive drugs (such as beta adrenergic blocking agents, cardiac glycosides, and calcium channel blockers) without apparent adverse interactions, but its effectiveness with these agents has not been systematically evaluated. Because of the potential for additive or synergistic depressant effects on the SA and AV nodes, however, adenosine should be used with caution in the presence of these agents [see Warnings and Precautions (5.2)].

8 USE IN SPECIFIC POPULATIONS

8.1 Pregnancy

Teratogenic Effects

Animal reproduction studies have not been conducted with adenosine; nor have studies been performed in pregnant women. Because it is not known whether adenosine can cause fetal harm when administered to pregnant women, adenosine should be used during pregnancy only if clearly needed.

8.3 Nursing Mothers

It is not known whether adenosine is excreted in human milk. Because many drugs are excreted in human milk and because of the potential for serious adverse reactions from adenosine in nursing infants, the decision to interrupt nursing after administration of adenosine or not to administer adenosine, should take into account the importance of the drug to the mother.

8.4 Pediatric Use

The safety and effectiveness of adenosine in patients less than 18 years of age have not been established.

8.5 Geriatric Use

Clinical studies with adenosine did not include sufficient numbers of subjects aged younger than 65 years to determine whether they respond differently. Other reported experience has not revealed clinically relevant differences of the response of elderly in comparison to younger patients.

10 OVERDOSAGE

The half-life of adenosine is less than 10 seconds and adverse reactions of adenosine usually resolve quickly when the infusion is discontinued, although delayed or persistent reactions have been observed. Methylxanthines, such as caffeine, aminophylline, and theophylline, are competitive adenosine receptor antagonists and theophylline has been used to terminate persistent adverse reactions. In clinical trials, theophylline (50 to 125 mg slow intravenous injection) was used to attenuate adenosine adverse reactions in approximately 2% of patients. Methylxanthine use is not recommended in patients who experience seizures in association with adenosine [see Drug Interactions (7.1)].

11 DESCRIPTION

Adenosine, USP is an endogenous nucleoside and is chemically described as 6-Amino-9-β-D-ribofuranosyl-9H-purine. Adenosine, USP has the following structural formula:

The molecular formula for adenosine, USP is C10 H13 N5 O4 and its molecular weight is 267.24.

Adenosine, USP is a white crystalline powder. It is soluble in water and practically insoluble in alcohol. Solubility increases by warming and lowering the pH of the solution.

Adenosine injection, USP is a sterile, non-pyrogenic, clear, colorless solution for intravenous use. Each mL of adenosine injection, USP contains adenosine USP, 3 mg and sodium chloride 9 mg in water for injection q.s. The pH of the solution is between 4.5 and 7.5.

12 CLINICAL PHARMACOLOGY

12.1 Mechanism of Action

Adenosine causes cardiac vasodilation which increases cardiac blood flow. Adenosine is thought to exert its pharmacological effects through activation of purine receptors (cell-surface A1 and A2 adenosine receptors). Although the exact mechanism by which adenosine receptor activation relaxes vascular smooth muscle is not known, there is evidence to support both inhibition of the slow inward calcium current reducing calcium uptake, and activation of adenylate cyclase through A2 receptors in smooth muscle cells. Adenosine may also lessen vascular tone by modulating sympathetic neurotransmission. The intracellular uptake of adenosine is mediated by a specific transmembrane nucleoside transport system. Once inside the cell, adenosine is rapidly phosphorylated by adenosine kinase to adenosine monophosphate, or deaminated by adenosine deaminase to inosine. These intracellular metabolites of adenosine are not vasoactive.
Myocardial uptake of thallium-201 is directly proportional to coronary blood flow. Since adenosine significantly increases blood flow in normal coronary arteries with little or no increase in stenotic arteries, adenosine causes relatively less thallium-201 uptake in vascular territories supplied by stenotic coronary arteries i.e., a greater difference is seen after adenosine between areas served by normal and areas served by stenotic vessels than is seen prior to adenosine.

12.2 Pharmacodynamics

Hemodynamic Effects
Adenosine produces a direct negative chronotropic, dromotropic and inotropic effect on the heart, presumably due to A1-receptor agonism, and produces peripheral vasodilation, presumably due to A2-receptor agonism. The net effect of adenosine in humans is typically a mild to moderate reduction in systolic, diastolic and mean arterial blood pressure associated with a reflex increase in heart rate. Rarely, significant hypotension and tachycardia have been observed [see Warnings and Precautions (5.4)].

12.3 Pharmacokinetics

Distribution
Intravenously administered adenosine distributes from the circulation via cellular uptake, primarily by erythrocytes and vascular endothelial cells. This process involves a specific transmembrane nucleoside carrier system that is reversible, nonconcentrative, and bidirectionally symmetrical.
Metabolism
Intracellular adenosine is metabolized either via phosphorylation to adenosine monophosphate by adenosine kinase, or via deamination to inosine by adenosine deaminase in the cytosol. Since adenosine kinase has a lower Km and Vmax than adenosine deaminase, deamination plays a significant role only when cytosolic adenosine saturates the phosphorylation pathway. Inosine formed by deamination of adenosine can leave the cell intact or can be degraded to hypoxanthine, xanthine, and ultimately uric acid. Adenosine monophosphate formed by phosphorylation of adenosine is incorporated into the high-energy phosphate pool.
Elimination
While extracellular adenosine is primarily cleared from plasma by cellular uptake with a half-life of less than 10 seconds in whole blood, excessive amounts may be deaminated by an ecto-form of adenosine deaminase.
Specific Populations
Renal Impairment
As adenosine does not require renal function for its activation or inactivation, renal impairment would not be expected to alter its effectiveness or tolerability.
Hepatic Impairment
As adenosine does not require hepatic function for its activation or inactivation, hepatic impairment would not be expected to alter its effectiveness or tolerability.

13 NONCLINICAL TOXICOLOGY

13.1 Carcinogenesis, Mutagenesis, Impairment of Fertility

Studies in animals have not been performed to evaluate adenosine’s carcinogenic potential or potential effects on fertility. Adenosine was negative for genotoxic potential in the Salmonella (Ames Test) and Mammalian Microsome Assay.

Adenosine, however, like other nucleosides at millimolar concentrations present for several doubling times of cells in culture, is known to produce a variety of chromosomal alterations.

14 CLINICAL STUDIES

In two crossover comparative studies involving 319 subjects who could exercise (including 106 healthy volunteers and 213 patients with known or suspected coronary disease), adenosine and exercise thallium images were compared by blinded observers. The images were concordant for the presence of perfusion defects in 85.5% of cases by global analysis (patient by patient) and up to 93% of cases based on vascular territories.

In the two studies, 193 patients also had recent coronary arteriography for comparison (healthy volunteers were not catheterized). The sensitivity for detecting angiographically significant disease (≥ 50% reduction in the luminal diameter of at least one major vessel) was 64% for adenosine and 64% for exercise testing. The specificity was 54% for adenosine and 65% for exercise testing. The 95% confidence limits for adenosine sensitivity were 56% to 78% and for specificity were 37% to 71%.

Intracoronary Doppler flow catheter studies have demonstrated that a dose of intravenous adenosine of 0.14 mg/kg/min produces maximum coronary hyperemia (relative to intracoronary papaverine) in approximately 95% of cases within two to three minutes of the onset of the infusion. Coronary blood flow velocity returns to basal levels within one to two minutes of discontinuing the adenosine infusion.

16 HOW SUPPLIED/STORAGE AND HANDLING

How Supplied

Adenosine injection, USP is supplied as 60 mg per 20 mL (3 mg per mL) and 90 mg per 30 mL (3 mg per mL) in single-dose vials of clear, colorless solution in normal saline.

NDC | Adenosine Injection, USP (3 mg per mL) | Package Factor
71288-207-21 | 60 mg per 20 mL Single-Dose Vial | 10 vials per carton
71288-208-30 | 90 mg per 30 mL Single-Dose Vial | 1 vial per carton

Storage and Handling

- Store at 20° to 25°C (68° to 77°F) [see USP Controlled Room Temperature].
- Do not refrigerate as crystallization may occur. If crystallization has occurred, dissolve crystals by warming to room temperature. The solution must be clear at the time of use
- Discard unused portion

Sterile, Nonpyrogenic, Preservative-free.

The container closure is not made with natural rubber latex.

17 PATIENT COUNSELING INFORMATION

- Advise patients that they may be at increased risk of fatal and nonfatal heart attacks, abnormal heart rhythms, cardiac arrest, heart block, significant increase or decrease in blood pressure, bronchoconstriction, hypersensitivity reactions, seizures, or cerebrovascular accidents with the use of adenosine [see Warnings and Precautions (5.1 to 5.9)].
- Advise patients with COPD or asthma to discuss their respiratory history with their clinician before scheduling a myocardial perfusion imaging study with adenosine [see Warnings and Precautions (5.3)].
- Methylxanthines have the potential to impact the effects of adenosine. Instruct patients to avoid consumption of any products containing methylxanthines, including caffeinated coffee, tea or other caffeinated beverages, caffeine- containing drug products, aminophylline, and theophylline prior to the myocardial perfusion imaging study. Question patients about a history of seizures [see Warnings and Precautions (5.6), Drug Interactions (7.1), and Overdosage (10)].

meitheal®

Mfd. for Meitheal Pharmaceuticals
Chicago, IL 60631 (USA)
©2024 Meitheal Pharmaceuticals Inc.

Mfd. by Nanjing King-Friend Biochemical Pharmaceutical Co., Ltd.
Nanjing, China 210061

October 2024

8S8ACM9-00

PRINCIPAL DISPLAY PANEL - Adenosine Injection, USP 60 mg per 20 mL Container Label

NDC 71288-207-20

Rx only

Adenosine Injection, USP

60 mg per 20 mL

(3 mg per mL)

FOR INTRAVENOUS INFUSION ONLY

Sterile, Nonpyrogenic

Discard Unused Portion

20 mL Single-Dose Vial

PRINCIPAL DISPLAY PANEL - Adenosine Injection, USP 60 mg per 20 mL Carton

NDC 71288-207-21

Rx only

Adenosine Injection, USP

60 mg per 20 mL

(3 mg per mL)

FOR INTRAVENOUS INFUSION ONLY

Discard Unused Portion

10 x 20 mL Single-Dose Vials

PRINCIPAL DISPLAY PANEL - Adenosine Injection, USP 90 mg per 30 mL Container Label

NDC 71288-208-30

Rx only

Adenosine Injection, USP

90 mg per 30 mL

(3 mg per mL)

FOR INTRAVENOUS INFUSION ONLY

Sterile, Nonpyrogenic

Discard Unused Portion

30 mL Single-Dose Vial

PRINCIPAL DISPLAY PANEL - Adenosine Injection, USP 90 mg per 30 mL Carton

NDC 71288-208-30

Rx only

Adenosine Injection, USP

90 mg per 30 mL

(3 mg per mL)

FOR INTRAVENOUS INFUSION ONLY

Discard Unused Portion

1 x 30 mL Single-Dose Vial